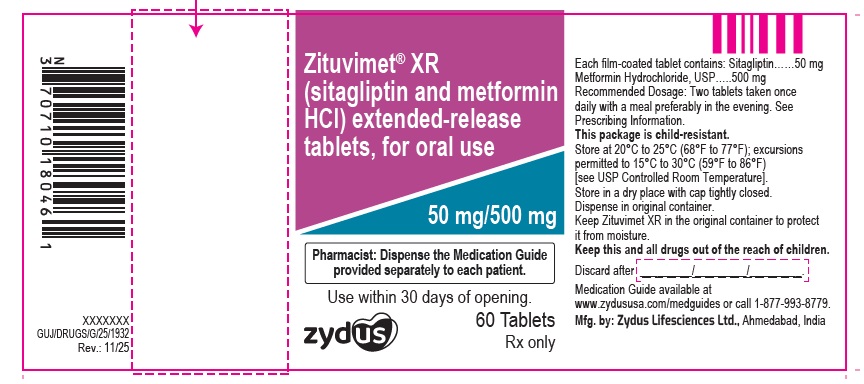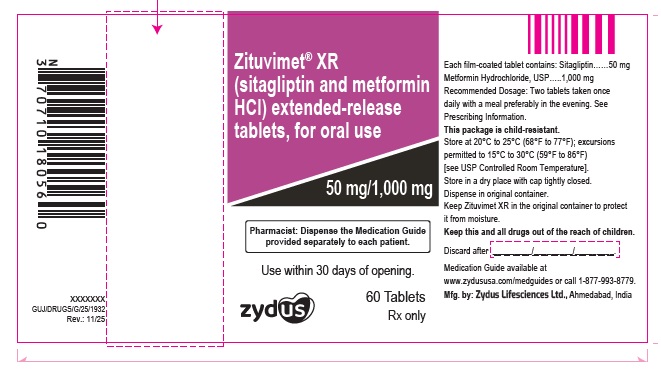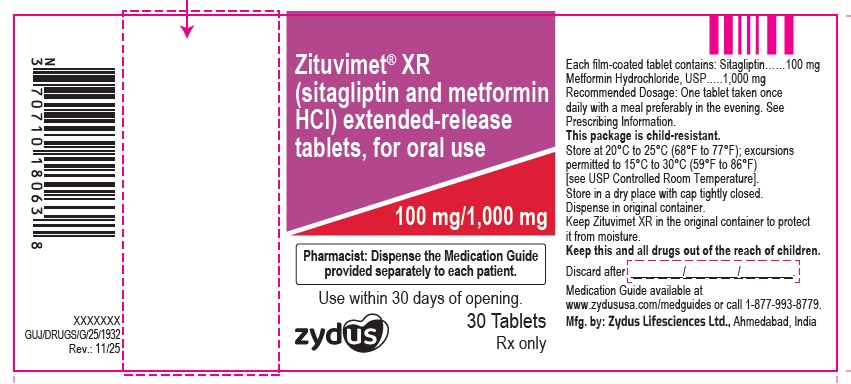 DRUG LABEL: ZITUVIMET XR
NDC: 70771-1880 | Form: TABLET, FILM COATED, EXTENDED RELEASE
Manufacturer: Zydus Lifesciences Limited
Category: prescription | Type: HUMAN PRESCRIPTION DRUG LABEL
Date: 20260105

ACTIVE INGREDIENTS: SITAGLIPTIN 50 mg/1 1; METFORMIN HYDROCHLORIDE 1000 mg/1 1
INACTIVE INGREDIENTS: ANHYDROUS DIBASIC CALCIUM PHOSPHATE; CROSCARMELLOSE SODIUM; FD&C YELLOW NO. 6; FERRIC OXIDE YELLOW; HYPROMELLOSE 2208 (100000 MPA.S); HYPROMELLOSE 2208 (200000 MPA.S); MAGNESIUM STEARATE; MALIC ACID; MICROCRYSTALLINE CELLULOSE; POLYETHYLENE GLYCOL, UNSPECIFIED; POLYVINYL ALCOHOL, UNSPECIFIED; POVIDONE; SILICON DIOXIDE; SODIUM STEARYL FUMARATE; STARCH, CORN; TALC; TITANIUM DIOXIDE

ZITUVIMET® XR (sitagliptin and metformin hydrochloride) extended-release tablets, for oral use

PACKAGE LABEL.PRINCIPAL DISPLAY PANEL

NDC 70771-1879-6

ZITUVIMET® XR (sitagliptin and metformin hydrochloride extended-release) tablets

50 mg/500 mg

60 Tablets

Rx only

NDC 70771-1880-6

ZITUVIMET® XR (sitagliptin and metformin hydrochloride extended-release) tablets

50 mg/1,000 mg

60 Tablets

Rx only

NDC 70771-1881-3

ZITUVIMET® XR (sitagliptin and metformin hydrochloride extended-release) tablets

100 mg/1,000 mg

30 Tablets

Rx only